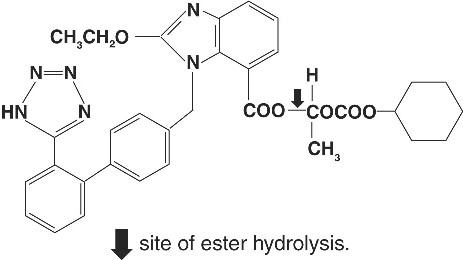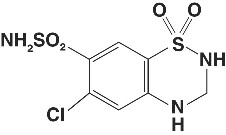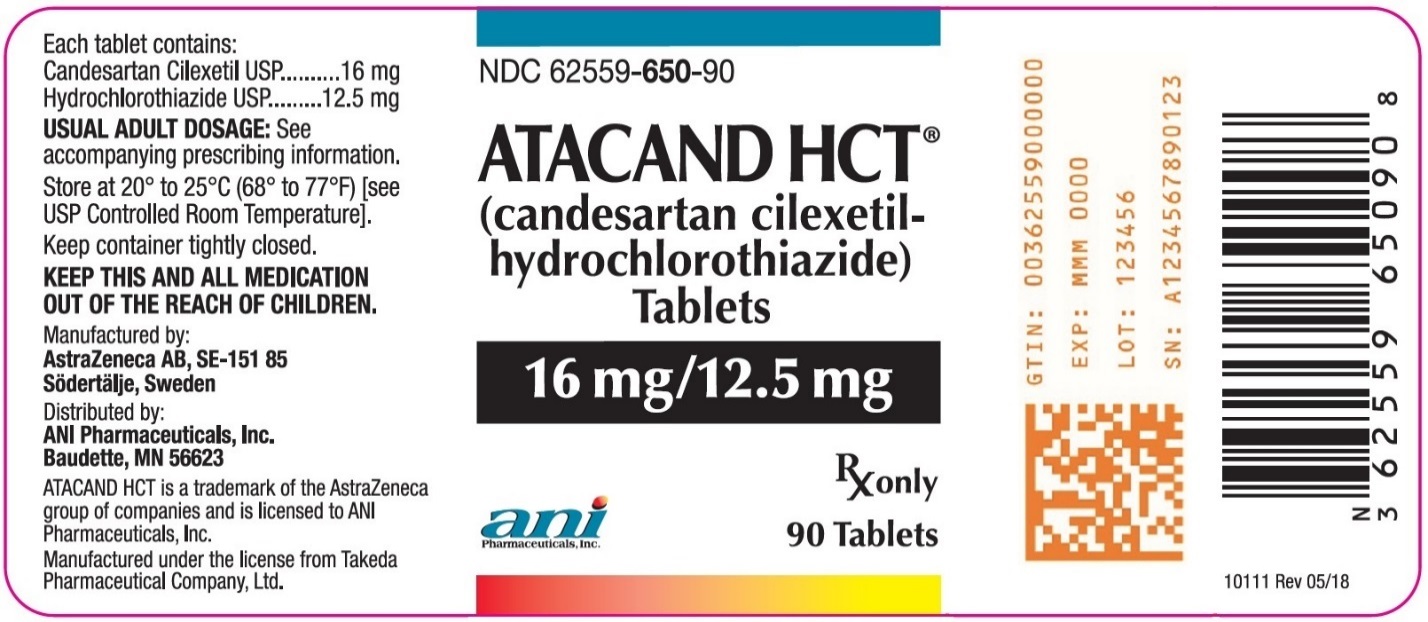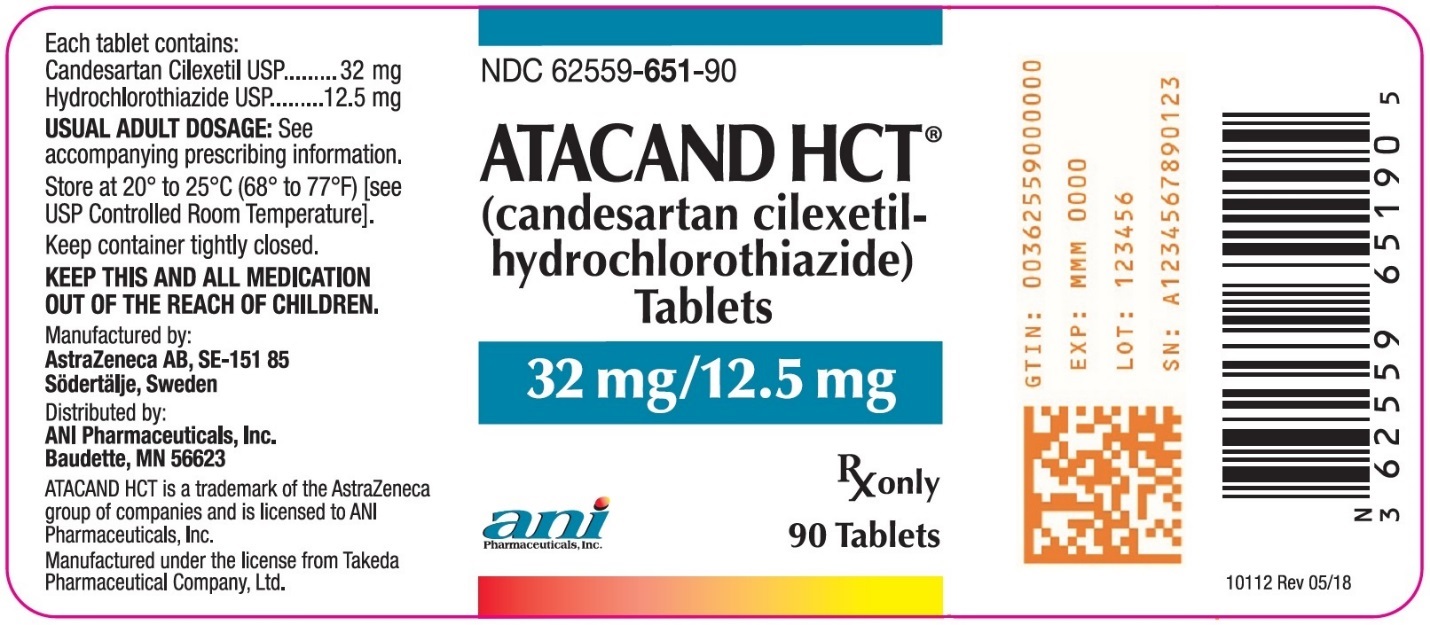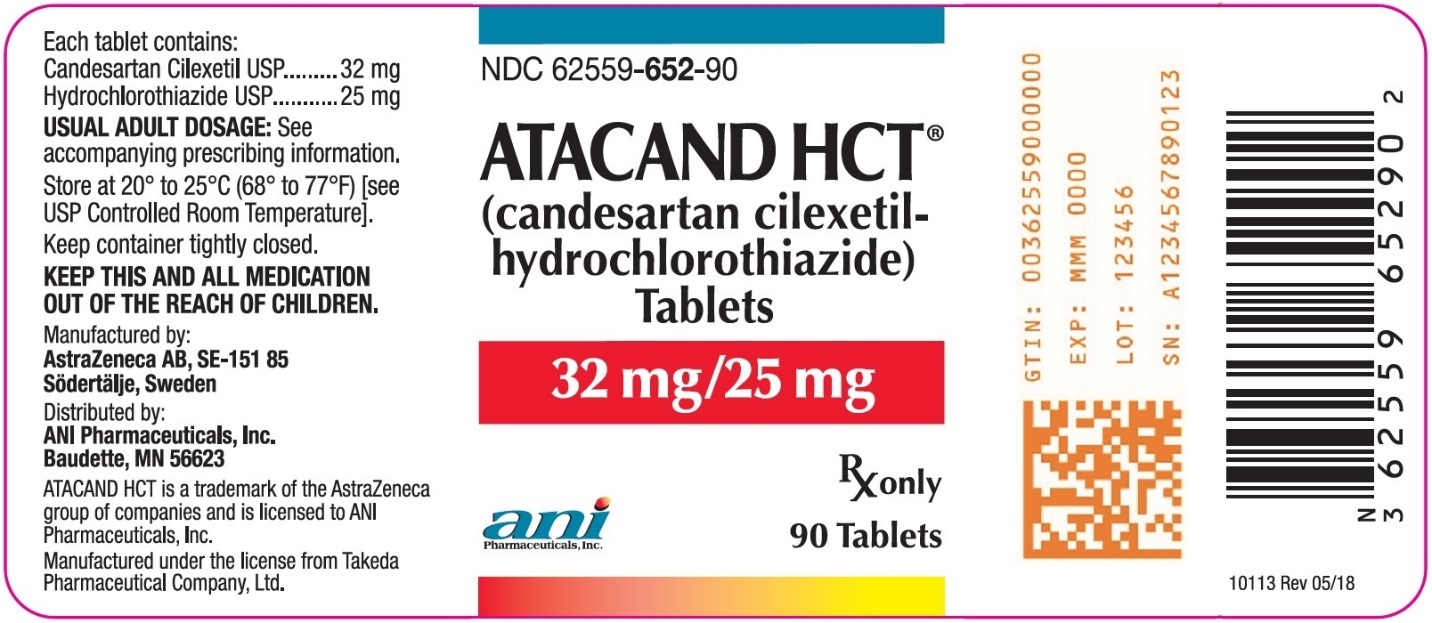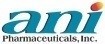 DRUG LABEL: ATACAND HCT
NDC: 62559-650 | Form: TABLET
Manufacturer: ANI Pharmaceuticals, Inc.
Category: prescription | Type: HUMAN PRESCRIPTION DRUG LABEL
Date: 20251222

ACTIVE INGREDIENTS: CANDESARTAN CILEXETIL 16 mg/1 1; HYDROCHLOROTHIAZIDE 12.5 mg/1 1
INACTIVE INGREDIENTS: CARBOXYMETHYLCELLULOSE CALCIUM; HYDROXYPROPYL CELLULOSE, UNSPECIFIED; LACTOSE MONOHYDRATE; MAGNESIUM STEARATE; STARCH, CORN; POLYETHYLENE GLYCOL 8000; FERRIC OXIDE YELLOW; FERRIC OXIDE RED

ATACAND HCT® 16-12.5
(candesartan cilexetil-hydrochlorothiazide)
TABLETS, FOR ORAL USE
ATACAND HCT® 32-12.5
(candesartan cilexetil-hydrochlorothiazide)
TABLETS, FOR ORAL USE
ATACAND HCT® 32-25
(candesartan cilexetil-hydrochlorothiazide)
TABLETS, FOR ORAL USE

WARNING: FETAL TOXICITY

- When pregnancy is detected, discontinue ATACAND HCT as soon as possible.
- Drugs that act directly on the renin-angiotensin system can cause injury and death to the developing fetus. See Warnings: Fetal Toxicity

DESCRIPTION

ATACAND HCT (candesartan cilexetil-hydrochlorothiazide) combines an angiotensin II receptor (type AT1) antagonist and a diuretic, hydrochlorothiazide.

Candesartan cilexetil, a nonpeptide, is chemically described as (±)-1-Hydroxyethyl 2-ethoxy-1-[p-(o-1H-tetrazol-5-ylphenyl)benzyl]-7-benzimidazolecarboxylate, cyclohexyl carbonate (ester).

Its empirical formula is C33H34N6O6 and its structural formula is:

Candesartan cilexetil is a white to off-white powder with a molecular weight of 610.67. It is practically insoluble in water and sparingly soluble in methanol. Candesartan cilexetil is a racemic mixture containing one chiral center at the cyclohexyloxycarbonyloxy ethyl ester group. Following oral administration, candesartan cilexetil undergoes hydrolysis at the ester link to form the active drug, candesartan, which is achiral.

Hydrochlorothiazide is 6-chloro-3,4-dihydro-2H-1,2,4-benzothiadiazine-7-sulfonamide 1,1-dioxide. Its empirical formula is C7H8ClN3O4S2 and its structural formula is:

Hydrochlorothiazide is a white, or practically white, crystalline powder with a molecular weight of 297.72, which is slightly soluble in water, but freely soluble in sodium hydroxide solution.

ATACAND HCT is available for oral administration in three tablet strengths of candesartan cilexetil and hydrochlorothiazide.

ATACAND HCT 16-12.5 contains 16 mg of candesartan cilexetil and 12.5 mg of hydrochlorothiazide. ATACAND HCT 32-12.5 contains 32 mg of candesartan cilexetil and 12.5 mg of hydrochlorothiazide. ATACAND HCT 32-25 contains 32 mg of candesartan cilexetil and 25 mg of hydrochlorothiazide. The inactive ingredients of the tablets are carboxymethylcellulose calcium, hydroxypropyl cellulose, lactose monohydrate, magnesium stearate, cornstarch, polyethylene glycol 8000, and ferric oxide (yellow). Ferric oxide (reddish brown) is also added to the 16-12.5 mg and 32-25 mg tablets as colorant.

CLINICAL PHARMACOLOGY

Mechanism of Action

Angiotensin II is formed from angiotensin I in a reaction catalyzed by angiotensin-converting enzyme (ACE, kininase II). Angiotensin II is the principal pressor agent of the renin-angiotensin system, with effects that include vasoconstriction, stimulation of synthesis and release of aldosterone, cardiac stimulation, and renal reabsorption of sodium. Candesartan blocks the vasoconstrictor and aldosterone-secreting effects of angiotensin II by selectively blocking the binding of angiotensin II to the AT1 receptor in many tissues, such as vascular smooth muscle and the adrenal gland. Its action is, therefore, independent of the pathways for angiotensin II synthesis.

There is also an AT2 receptor found in many tissues, but AT2 is not known to be associated with cardiovascular homeostasis. Candesartan has much greater affinity (>10,000-fold) for the AT1 receptor than for the AT2 receptor.

Blockade of the renin-angiotensin system with ACE inhibitors, which inhibit the biosynthesis of angiotensin II from angiotensin I, is widely used in the treatment of hypertension. ACE inhibitors also inhibit the degradation of bradykinin, a reaction also catalyzed by ACE. Because candesartan does not inhibit ACE (kininase II), it does not affect the response to bradykinin. Whether this difference has clinical relevance is not yet known. Candesartan does not bind to or block other hormone receptors or ion channels known to be important in cardiovascular regulation.

Blockade of the angiotensin II receptor inhibits the negative regulatory feedback of angiotensin II on renin secretion, but the resulting increased plasma renin activity and angiotensin II circulating levels do not overcome the effect of candesartan on blood pressure.

Hydrochlorothiazide is a thiazide diuretic. Thiazides affect the renal tubular mechanisms of electrolyte reabsorption, directly increasing excretion of sodium and chloride in approximately equivalent amounts. Indirectly, the diuretic action of hydrochlorothiazide reduces plasma volume, with consequent increases in plasma renin activity, increases in aldosterone secretion, increases in urinary potassium loss, and decreases in serum potassium. The renin-aldosterone link is mediated by angiotensin II, so co‑administration of an angiotensin II receptor antagonist tends to reverse the potassium loss associated with these diuretics.

The mechanism of the antihypertensive effect of thiazides is unknown.

Pharmacokinetics

General

Candesartan Cilexetil

Candesartan cilexetil is rapidly and completely bioactivated by ester hydrolysis during absorption from the gastrointestinal tract to candesartan, a selective AT1 subtype angiotensin II receptor antagonist. Candesartan is mainly excreted unchanged in urine and feces (via bile). It undergoes minor hepatic metabolism by O-deethylation to an inactive metabolite. The elimination half-life of candesartan is approximately 9 hours. After single and repeated administration, the pharmacokinetics of candesartan are linear for oral doses up to 32 mg of candesartan cilexetil. Candesartan and its inactive metabolite do not accumulate in serum upon repeated once-daily dosing.

Following administration of candesartan cilexetil, the absolute bioavailability of candesartan was estimated to be 15%. After tablet ingestion, the peak serum concentration (Cmax) is reached after 3 to 4 hours. Food with a high fat content does not affect the bioavailability of candesartan after candesartan cilexetil administration.

Hydrochlorothiazide

When plasma levels have been followed for at least 24 hours, the plasma half-life has been observed to vary between 5.6 and 14.8 hours.

Metabolism and Excretion

Candesartan Cilexetil

Total plasma clearance of candesartan is 0.37 mL/min/kg, with a renal clearance of 0.19 mL/min/kg. When candesartan is administered orally, about 26% of the dose is excreted unchanged in urine. Following an oral dose of ^14C-labeled candesartan cilexetil, approximately 33% of radioactivity is recovered in urine and approximately 67% in feces. Following an intravenous dose of ^14C-labeled candesartan, approximately 59% of radioactivity is recovered in urine and approximately 36% in feces. Biliary excretion contributes to the elimination of candesartan.

Hydrochlorothiazide

Hydrochlorothiazide is not metabolized but is eliminated rapidly by the kidney. At least 61% of the oral dose is eliminated unchanged within 24 hours.

Distribution

Candesartan Cilexetil

The volume of distribution of candesartan is 0.13 L/kg. Candesartan is highly bound to plasma proteins (>99%) and does not penetrate red blood cells. The protein binding is constant at candesartan plasma concentrations well above the range achieved with recommended doses. In rats, it has been demonstrated that candesartan crosses the blood-brain barrier poorly, if at all. It has also been demonstrated in rats that candesartan passes across the placental barrier and is distributed in the fetus.

Hydrochlorothiazide

Hydrochlorothiazide crosses the placental but not the blood-brain barrier and is excreted in breast milk.

Special Populations

Pediatric

The pharmacokinetics of candesartan cilexetil have not been investigated in patients <18 years of age.

Geriatric

The pharmacokinetics of candesartan have been studied in the elderly (≥ 65 years). The plasma concentration of candesartan was higher in the elderly (Cmax was approximately 50% higher, and AUC was approximately 80% higher) compared to younger subjects administered the same dose. The pharmacokinetics of candesartan were linear in the elderly, and candesartan and its inactive metabolite did not accumulate in the serum of these subjects upon repeated, once-daily administration. No initial dosage adjustment is necessary (see DOSAGE AND ADMINISTRATION).

Gender

There is no difference in the pharmacokinetics of candesartan between male and female subjects.

Renal Insufficiency

In hypertensive patients with renal insufficiency, serum concentrations of candesartan were elevated. After repeated dosing, the AUC and Cmax were approximately doubled in patients with severe renal impairment (creatinine clearance <30 mL/min/1.73m^2) compared to patients with normal kidney function. The pharmacokinetics of candesartan in hypertensive patients undergoing hemodialysis are similar to those in hypertensive patients with severe renal impairment. Candesartan cannot be removed by hemodialysis.

Thiazide diuretics are eliminated by the kidney, with a terminal half-life of 5-15 hours. In a study of patients with impaired renal function (mean creatinine clearance of 19 mL/min), the half-life of hydrochlorothiazide elimination was lengthened to 21 hours (see DOSAGE AND ADMINISTRATION).

Safety and effectiveness of ATACAND HCT in patients with severe renal impairment (CrCL ≤30 ml/min) have not been established. No dose adjustment is required in patients with mild (CrCL 60-90 ml/min) or moderate (CrCL 30-60 ml/min) renal impairment.

Hepatic Insufficiency

The pharmacokinetics of candesartan were compared in patients with mild (Child-Pugh A) or moderate (Child-Pugh B) hepatic impairment to matched healthy volunteers following a single dose of 16 mg candesartan cilexetil. The AUC for candesartan in patients with mild and moderate hepatic impairment was increased 30% and 145% respectively. The Cmax for candesartan was increased 56% and 73% respectively. The pharmacokinetics of candesartan in severe hepatic impairment have not been studied. No dose adjustment is recommended for patients with mild hepatic impairment. In patients with moderate hepatic impairment, ATACAND HCT is not recommended for initiation because the appropriate starting dose, 8 mg, cannot be given (see DOSAGE AND ADMINISTRATION).

Monitor patients with impaired hepatic function or progressive liver disease, since minor alterations of fluid and electrolyte balance may precipitate hepatic coma.

Pharmacodynamics

Candesartan Cilexetil

Candesartan inhibits the pressor effects of angiotensin II infusion in a dose-dependent manner. After 1 week of once-daily dosing with 8 mg of candesartan cilexetil, the pressor effect was inhibited by approximately 90% at peak with approximately 50% inhibition persisting for 24 hours.

Plasma concentrations of angiotensin I and angiotensin II, and plasma renin activity (PRA), increased in a dose-dependent manner after single and repeated administration of candesartan cilexetil to healthy subjects and hypertensive patients. ACE activity was not altered in healthy subjects after repeated candesartan cilexetil administration. The once-daily administration of up to 16 mg of candesartan cilexetil to healthy subjects did not influence plasma aldosterone concentrations, but a decrease in the plasma concentration of aldosterone was observed when 32 mg of candesartan cilexetil was administered to hypertensive patients. In spite of the effect of candesartan cilexetil on aldosterone secretion, very little effect on serum potassium was observed.

In multiple-dose studies with hypertensive patients, there were no clinically significant changes in metabolic function including serum levels of total cholesterol, triglycerides, glucose, or uric acid. In a 12-week study of 161 patients with non-insulin-dependent (type 2) diabetes mellitus and hypertension, there was no change in the level of HbA1c.

Hydrochlorothiazide

After oral administration of hydrochlorothiazide, diuresis begins within 2 hours, peaks in about 4 hours and lasts about 6 to 12 hours.

Clinical Trials

Candesartan Cilexetil−Hydrochlorothiazide

Of 12 controlled clinical trials involving 4588 patients, 5 were double-blind, placebo controlled and evaluated the antihypertensive effects of single entities vs the combination. These 5 trials, of 8 to 12 weeks duration, randomized 3037 hypertensive patients. Doses ranged from 2 to 32 mg candesartan cilexetil and from 6.25 to 25 mg hydrochlorothiazide administered once daily in various combinations.

The combination of candesartan cilexetil-hydrochlorothiazide resulted in placebo-adjusted decreases in sitting systolic and diastolic blood pressures of 14-18/8-11 mm Hg at doses of 16-12.5 mg and 32-12.5 mg. The combination of candesartan cilexetil and hydrochlorothiazide 32-25 mg resulted in placebo-adjusted decreases in sitting systolic and diastolic blood pressures of 16-19/9-11 mm Hg. The placebo corrected trough to peak ratio was evaluated in a study of candesartan cilexetil-hydrochlorothiazide 32-12.5 mg and was 88%.

Most of the antihypertensive effect of the combination of candesartan cilexetil and hydrochlorothiazide was seen in 1 to 2 weeks with the full effect observed within 4 weeks. In long-term studies of up to 1 year, the blood pressure lowering effect of the combination was maintained. The antihypertensive effect was similar regardless of age or gender, and overall response to the combination was similar in black and non-black patients. No appreciable changes in heart rate were observed with combination therapy in controlled trials.

INDICATIONS AND USAGE

ATACAND HCT is indicated for the treatment of hypertension, to lower blood pressure. Lowering blood pressure reduces the risk of fatal and non-fatal cardiovascular events, primarily strokes and myocardial infarctions. These benefits have been seen in controlled trials of antihypertensive drugs from a wide variety of pharmacologic classes including the class to which this drug principally belongs. There are no controlled trials demonstrating risk reduction with ATACAND HCT.

Control of high blood pressure should be part of comprehensive cardiovascular risk management, including, as appropriate, lipid control, diabetes management, antithrombotic therapy, smoking cessation, exercise, and limited sodium intake. Many patients will require more than one drug to achieve blood pressure goals. For specific advice on goals and management, see published guidelines, such as those of the National High Blood Pressure Education Program’s Joint National Committee on Prevention, Detection, Evaluation, and Treatment of High Blood Pressure (JNC).

Numerous antihypertensive drugs, from a variety of pharmacologic classes and with different mechanisms of action, have been shown in randomized controlled trials to reduce cardiovascular morbidity and mortality, and it can be concluded that it is blood pressure reduction, and not some other pharmacologic property of the drugs, that is largely responsible for those benefits. The largest and most consistent cardiovascular outcome benefit has been a reduction in the risk of stroke, but reductions in myocardial infarction and cardiovascular mortality also have been seen regularly.

Elevated systolic or diastolic pressure causes increased cardiovascular risk, and the absolute risk increase per mmHg is greater at higher blood pressures, so that even modest reductions of severe hypertension can provide substantial benefit. Relative risk reduction from blood pressure reduction is similar across populations with varying absolute risk, so the absolute benefit is greater in patients who are at higher risk independent of their hypertension (for example, patients with diabetes or hyperlipidemia), and such patients would be expected to benefit from more aggressive treatment to a lower blood pressure goal.

Some antihypertensive drugs have smaller blood pressure effects (as monotherapy) in black patients, and many antihypertensive drugs have additional approved indications and effects (e.g., on angina, heart failure, or diabetic kidney disease). These considerations may guide selection of therapy.

This fixed dose combination is not indicated for initial therapy (see DOSAGE AND ADMINISTRATION).

CONTRAINDICATIONS

ATACAND HCT is contraindicated in patients who are hypersensitive to candesartan, to hydrochlorothiazide or to other sulfonamide-derived drugs.

Do not co-administer aliskiren with ATACAND HCT in patients with diabetes (see PRECAUTIONS, Drug Interactions).

ATACAND HCT is contraindicated in patients with anuria.

WARNINGS

Fetal Toxicity

Use of drugs that act on the renin-angiotensin system during the second and third trimesters of pregnancy reduces fetal renal function and increases fetal and neonatal morbidity and death. Resulting oligohydramnios can be associated with fetal lung hypoplasia and skeletal deformations. Potential neonatal adverse effects include skull hypoplasia, anuria, hypotension, renal failure, and death. When pregnancy is detected, discontinue ATACAND HCT as soon as possible. These adverse outcomes are usually associated with use of these drugs in the second and third trimester of pregnancy. Most epidemiologic studies examining fetal abnormalities after exposure to antihypertensive use in the first trimester have not distinguished drugs affecting the renin-angiotensin system from other antihypertensive agents. Appropriate management of maternal hypertension during pregnancy is important to optimize outcomes for both mother and fetus.

In the unusual case that there is no appropriate alternative to therapy with drugs affecting the renin-angiotensin system for a particular patient, apprise the mother of the potential risk to the fetus. Perform serial ultrasound examinations to assess the intra-amniotic environment. If oligohydramnios is observed, discontinue ATACAND HCT, unless it is considered lifesaving for the mother. Fetal testing may be appropriate, based on the week of pregnancy. Patients and physicians should be aware, however, that oligohydramnios may not appear until after the fetus has sustained irreversible injury. Closely observe infants with histories of in utero exposure to ATACAND HCT for hypotension, oliguria, and hyperkalemia (see PRECAUTIONS, Pediatric Use).

There was no evidence of teratogenicity or other adverse effects on embryo-fetal development when pregnant mice, rats or rabbits were treated orally with candesartan cilexetil alone or in combination with hydrochlorothiazide. For mice, the maximum dose of candesartan cilexetil was 1000 mg/kg/day (about 150 times the maximum recommended daily human dose [MRHD] [Doses compared on the basis of body surface area. MRHD considered to be 32 mg for candesartan cilexetil and 12.5 mg for hydrochlorothiazide.]). For rats, the maximum dose of candesartan cilexetil was 100 mg/kg/day (about 31 times the MRHD^1). For rabbits, the maximum dose of candesartan cilexetil was 1 mg/kg/day (a maternally toxic dose that is about half the MRHD^1). In each of these studies, hydrochlorothiazide was tested at the same dose level (10 mg/kg/day, about 4, 8, and 15 times the MRHD^1 in mouse, rats, and rabbit, respectively). There was no evidence of harm to the rat or mouse fetus or embryo in studies in which hydrochlorothiazide was administered alone to the pregnant rat or mouse at doses of up to 1000 and 3000 mg/kg/day, respectively.

Thiazides cross the placental barrier and appear in cord blood. There is a risk of fetal or neonatal jaundice, thrombocytopenia, and possibly other adverse reactions that have occurred in adults.

Hypotension

ATACAND HCT can cause symptomatic hypotension. Symptomatic hypotension is most likely to occur in patients who have been volume and/or salt depleted as a result of prolonged diuretic therapy, dietary salt restriction, dialysis, diarrhea, or vomiting. Patients with symptomatic hypotension may require temporarily reducing the dose of ATACAND HCT or volume repletion. Volume and/or salt depletion should be corrected before initiating therapy with ATACAND HCT.

In patients with heart failure, ATACAND HCT may cause excessive hypotension, which may lead to oliguria, azotemia, and (rarely) with acute renal failure and death (see WARNINGS, Impaired Renal Function). In such patients, ATACAND HCT therapy should be started under close medical supervision; they should be followed closely for the first 2 weeks of treatment and whenever the dose of candesartan or diuretic is increased.

Impaired Renal Function

Monitor renal function periodically in patients treated with ATACAND HCT. Changes in renal function including acute renal failure can be caused by drugs that inhibit the renin-angiotensin system and by diuretics. Patients whose renal function may depend in part on the activity of the renin-angiotensin system (e.g., patients with renal artery stenosis, chronic kidney disease, severe heart failure, or volume depletion) may be at particular risk of developing oliguria, progressive azotemia, or acute renal failure on ATACAND HCT. Consider withholding or discontinuing therapy in patients who develop a clinically significant decrease in renal function on ATACAND HCT.

Potassium Abnormalities

Drugs that inhibit the renin-angiotensin system can cause hyperkalemia. Hydrochlorothiazide can cause hypokalemia and hyponatremia. Hypomagnesemia can result in hypokalemia, which appears difficult to treat despite potassium repletion. Monitor serum electrolytes periodically.

In clinical trials of various doses of candesartan cilexetil and hydrochlorothiazide, the incidence of hypertensive patients who developed hypokalemia (serum potassium <3.5 mEq/L) was 2.5% versus 2.1% for placebo; the incidence of hyperkalemia (serum potassium >5.7 mEq/L) was 0.4% versus 1.0% for placebo. No patient receiving ATACAND HCT 16-12.5 mg or 32-12.5 mg was discontinued due to increases or decreases in serum potassium.

Acute Myopia and Secondary Angle-Closure Glaucoma

Hydrochlorothiazide, a sulfonamide, can cause an idiosyncratic reaction, resulting in acute transient myopia and acute angle-closure glaucoma. Symptoms include acute onset of decreased visual acuity or ocular pain and typically occur within hours to weeks of drug initiation. Untreated acute angle-closure glaucoma can lead to permanent vision loss. The primary treatment is to discontinue hydrochlorothiazide as rapidly as possible. Prompt medical or surgical treatments may need to be considered if the intraocular pressure remains uncontrolled. Risk factors for developing acute angle-closure glaucoma may include a history of sulfonamide or penicillin allergy.

Hypersensitivity Reaction

Hypersensitivity reactions to hydrochlorothiazide may occur in patients with or without a history of allergy or bronchial asthma, but are more likely in patients with such a history.

PRECAUTIONS

Metabolic Disturbances

Hydrochlorothiazide may alter glucose tolerance and raise serum levels of cholesterol and triglycerides.

Hydrochlorothiazide may raise the serum uric acid level due to reduced clearance of uric acid and may cause or exacerbate hyperuricemia and precipitate gout in susceptible patients.

Thiazides decrease urinary calcium excretion and may cause elevation of serum calcium. Avoid using ATACAND HCT in patients with hypercalcemia.

Systemic Lupus Erythematosus

Thiazide diuretics have been reported to cause exacerbation or activation of systemic lupus erythematosus.

Information for Patients

Pregnancy

Female patients of childbearing age should be told about the consequences of exposure to ATACAND HCT during pregnancy. Discuss treatment options with women planning to become pregnant. Patients should be asked to report pregnancies to their physicians as soon as possible.

Symptomatic Hypotension

Tell patients receiving ATACAND HCT that lightheadedness can occur, especially during the first days of therapy, and that it should be reported to the prescribing physician. Tell patients that if syncope occurs, discontinue ATACAND HCT until the physician has been consulted.

Tell all patients that inadequate fluid intake, excessive perspiration, diarrhea, or vomiting can lead to an excessive fall in blood pressure, with the same consequences of lightheadedness and possible syncope.

Hyperkalemia

Tell patients receiving ATACAND HCT not to use potassium supplements, salt substitutes containing potassium, or other drugs that may increase serum potassium levels without consulting the prescribing physician.

Non-melanoma Skin Cancer

Instruct patients taking hydrochlorothiazide to protect skin from the sun and undergo regular skin cancer screening.

Drug Interactions

Because candesartan is not significantly metabolized by the cytochrome P450 system and at therapeutic concentrations has no effects on P450 enzymes, interactions with drugs that inhibit or are metabolized by those enzymes would not be expected.

Interactions common to both Candesartan Cilexetil and Hydrochlorothiazide

Non-Steroidal Anti-Inflammatory Agents including Selective Cyclooxygenase-2 Inhibitors (COX-2 Inhibitors)

In patients who are elderly, volume-depleted (including those on diuretic therapy), or with compromised renal function, co-administration of NSAIDs, including selective COX-2 inhibitors, with angiotensin II receptor antagonists, including candesartan, may result in deterioration of renal function, including possible acute renal failure. These effects are usually reversible. Monitor renal function periodically in patients receiving candesartan and NSAID therapy.

The antihypertensive effect of angiotensin II receptor antagonists, including candesartan may be attenuated by NSAIDs including selective COX-2 inhibitors.

Lithium

Increases in serum lithium concentrations and lithium toxicity have been reported during concomitant administration of lithium with angiotensin II receptor antagonists or hydrochlorothiazide. Monitor serum lithium levels during concomitant use.

Interactions with Candesartan Cilexetil

Dual Blockade of the Renin-Angiotensin System (RAS)

Dual blockade of the RAS with angiotensin receptor blockers, ACE inhibitors, or aliskiren is associated with increased risks of hypotension, hyperkalemia, and changes in renal function (including acute renal failure) compared to monotherapy. Closely monitor blood pressure, renal function and electrolytes in patients on ATACAND HCT and other agents that affect the RAS.

Co-administration of ATACAND HCT with potassium sparing diuretics, potassium supplements, potassium-containing salt substitutes or other drugs that raise serum potassium levels may result in hyperkalemia. Monitor serum potassium in such patients.

Do not co-administer aliskiren with ATACAND HCT in patients with diabetes. Avoid use of aliskiren with ATACAND HCT in patients with renal impairment (GFR <60 mL/min) (see CONTRAINDICATIONS).

Interactions with Hydrochlorothiazide

Alcohol, barbiturates, or narcotics − Potentiation of orthostatic hypotension may occur.

Antidiabetic drugs (oral agents and insulin) − Dosage adjustment of the antidiabetic drug may be required.
Diazoxide − the hyperglycemic effect of diazoxide may be enhanced by thiazides.

Ion Exchange resins − Single doses of either cholestyramine or colestipol resins bind the hydrochlorothiazide and reduce its absorption from the gastrointestinal tract by up to 85% and 43%, respectively. Stagger the dosage of hydrochlorothiazide and ion exchange resins such that hydrochlorothiazide is administered at least 4 hours before or 4-6 hours after the administration of resins.

Skeletal muscle relaxants, nondepolarizing (e.g., tubocurarine) − Possible increased responsiveness to muscle relaxants such as curare derivatives.

Digitalis − Thiazide-induced hypokalemia or hypomagnesemia may predispose to digoxin toxicity.
Noradrenaline – Thiazides may decrease arterial responsiveness to noradrenaline, but not enough to preclude effectiveness of the pressor agent for therapeutic use.

Steroids or Adrenocorticotropic Hormone – Hypokalemia may develop during concomitant use of steroids or adrenocorticotropic hormone (ACTH).

Cytotoxic products – Thiazides may reduce the renal excretion of cytotoxic medicinal products (e.g. cyclophosphamide, methotrexate) and potentiate their myelosuppressive effects.

Cyclosporine − Concomitant treatment with cyclosporine may increase the risk of hyperuricemia and gout-type complications.

Carcinogenesis, Mutagenesis, Impairment of Fertility

No carcinogenicity studies have been conducted with the combination of candesartan cilexetil and hydrochlorothiazide. There was no evidence of carcinogenicity when candesartan cilexetil was orally administered to mice and rats for up to 104 weeks at doses up to 100 and 1000 mg/kg/day, respectively. Rats received the drug by gavage whereas mice received the drug by dietary administration. These (maximally-tolerated) doses of candesartan cilexetil provided systemic exposures to candesartan (AUCs) that were, in mice, approximately 7 times and, in rats, more than 70 times the exposure in man at the maximum recommended daily human dose (32 mg). Two-year feeding studies in mice and rats conducted under the auspices of the National Toxicology Program (NTP) uncovered no evidence of a carcinogenic potential of hydrochlorothiazide in female mice (at doses of up to approximately 600 mg/kg/day) or in male and female rats (at doses of up to approximately 100 mg/kg/day). The NTP, however, found equivocal evidence for hepatocarcinogenicity in male mice.

Candesartan cilexetil or candesartan (the active metabolite), in combination with hydrochlorothiazide, tested positive in vitro in the Chinese hamster lung (CHL) chromosomal aberration assay and mouse lymphoma mutagenicity assay. The candesartan cilexetil/hydrochlorothiazide combination tested negative for mutagenicity in bacteria (Ames test), for unscheduled DNA synthesis in rat liver, for chromosomal aberrations in rat bone marrow and for micronuclei in mouse bone marrow.

Both candesartan and its O-deethyl metabolite tested positive for genotoxicity in the in vitro CHL chromosomal aberration assay. Neither compound tested positive in the Ames microbial mutagenesis assay or in the in vitro mouse lymphoma cell assay. Candesartan (but not its O-deethyl metabolite) was also evaluated in vivo in the mouse micronucleus test and in vitro in the Chinese hamster ovary (CHO) gene mutation assay, in both cases with negative results. Candesartan cilexetil was evaluated in the Ames test, the in vitro mouse lymphoma cell assay, the in vivo rat hepatocyte unscheduled DNA synthesis assay and the in vivo mouse micronucleus test, in each case with negative results. Candesartan cilexetil was not evaluated in the CHL chromosomal aberration or CHO gene mutation assays.

When hydrochlorothiazide was tested alone, positive results were obtained in vitro in the CHO sister chromatid exchange (clastogenicity) and mouse lymphoma cell (mutagenicity) assays and in the Aspergillus nidulans non-disjunction assay. Hydrochlorothiazide was not genotoxic in vitro in the Ames test for point mutations and the CHO test for chromosomal aberrations, or in vivo in assays using mouse germinal cell chromosomes, Chinese hamster bone marrow chromosomes, and the Drosophila sex-linked recessive lethal trait gene.

No fertility studies have been conducted with the combination of candesartan cilexetil and hydrochlorothiazide. Fertility and reproductive performance were not affected in studies with male and female rats given oral doses of up to 300 mg candesartan cilexetil/kg/day (83 times the maximum daily human dose of 32 mg on a body surface area basis). Hydrochlorothiazide had no adverse effects on the fertility of mice and rats of either sex in studies wherein these species were exposed, via their diet, to doses of up to 100 and 4 mg/kg, respectively, prior to conception and throughout gestation.

Nursing Mothers

It is not known whether candesartan is excreted in human milk, but candesartan has been shown to be present in rat milk. Thiazides appear in human milk. Because of the potential for adverse effects on the nursing infant, a decision should be made whether to discontinue nursing or discontinue the drug, taking into account the importance of the drug to the mother.

Pediatric Use

Neonates with a history of in utero exposure to ATACAND HCT:

If oliguria or hypotension occurs, direct attention toward support of blood pressure and renal perfusion. Exchange transfusions or dialysis may be required as a means of reversing hypotension and/or substituting for disordered renal function.

Safety and effectiveness in pediatric patients have not been established.

ADVERSE REACTIONS

Candesartan Cilexetil-Hydrochlorothiazide

ATACAND HCT has been evaluated for safety in more than 2800 patients treated for hypertension. More than 750 of these patients were studied for at least six months and more than 500 patients were treated for at least one year. Adverse experiences have generally been mild and transient in nature and have only infrequently required discontinuation of therapy. The overall incidence of adverse events reported with ATACAND HCT was comparable to placebo. The overall frequency of adverse experiences was not related to dose, age, gender, or race.

In placebo-controlled trials that included 1089 patients treated with various combinations of candesartan cilexetil (doses of 2-32 mg) and hydrochlorothiazide (doses of 6.25-25 mg) and 592 patients treated with placebo, adverse events, whether or not attributed to treatment, occurring in greater than 2% of patients treated with ATACAND HCT and that were more frequent for ATACAND HCT than placebo were: Respiratory System Disorder: upper respiratory tract infection (3.6% vs 3.0%); Body as a Whole: back pain (3.3% vs 2.4%); influenza-like symptoms (2.5% vs 1.9%); Central/Peripheral Nervous System: dizziness (2.9% vs 1.2%).

Post-Marketing Experience

The following have been very rarely reported in post-marketing experience with candesartan cilexetil:

Digestive: Abnormal hepatic function and hepatitis.

Hematologic: Neutropenia, leukopenia, and agranulocytosis.

Immunologic: Angioedema

Metabolic and Nutritional Disorders: Hyperkalemia, hyponatremia.

Respiratory System Disorders: Cough

Skin and Appendages Disorders: Pruritus, rash and urticaria.

Rare reports of rhabdomyolysis have been reported in patients receiving angiotensin II receptor blockers.

Hydrochlorothiazide

Other adverse experiences that have been reported with hydrochlorothiazide, without regard to causality, are listed below:

Gastrointestinal: pancreatitis, jaundice (intrahepatic cholestatic jaundice), sialadenitis, cramping, constipation, gastric irritation, anorexia

Hematologic: aplastic anemia, agranulocytosis, leukopenia, hemolytic anemia, thrombocytopenia

Hypersensitivity: anaphylactic reactions, necrotizing angiitis (vasculitis and cutaneous vasculitis), respiratory distress including pneumonitis and pulmonary edema, photosensitivity, urticaria, purpura

Musculoskeletal: muscle spasm

Non-melanoma Skin Cancer: Hydrochlorothiazide is associated with an increased risk of non-melanoma skin cancer. In a study conducted in the Sentinel System, increased risk was predominantly for squamous cell carcinoma (SCC) and in white patients taking large cumulative doses. The increased risk for SCC in the overall population was approximately 1 additional case per 16,000 patients per year, and for white patients taking a cumulative dose of ≥50,000 mg the risk increase was approximately 1 additional SCC case for every 6,700 patients per year.

Skin: erythema multiforme including Stevens-Johnson syndrome, exfoliative dermatitis including toxic epidermal necrolysis, alopecia

Special Senses: transient blurred vision, xanthopsia

Urogenital: impotence

To report SUSPECTED ADVERSE REACTIONS, contact ANI Pharmaceuticals, Inc. at 1-855-204-1431 or FDA at 1-800-FDA-1088 or www.fda.gov/medwatch.

OVERDOSAGE

Candesartan Cilexetil-Hydrochlorothiazide

No lethality was observed in acute toxicity studies in mice, rats and dogs given single oral doses of up to 2000 mg/kg of candesartan cilexetil or in rats given single oral doses of up to 2000 mg/kg of candesartan cilexetil in combination with 1000 mg/kg of hydrochlorothiazide. In mice given single oral doses of the primary metabolite, candesartan, the minimum lethal dose was greater than 1000 mg/kg but less than 2000 mg/kg.

Limited data are available in regard to overdosage with candesartan cilexetil in humans. The most likely manifestations of overdosage with candesartan cilexetil would be hypotension, dizziness, and tachycardia; bradycardia could occur from parasympathetic (vagal) stimulation. If symptomatic hypotension should occur, supportive treatment should be initiated. For hydrochlorothiazide, the most common signs and symptoms observed are those caused by electrolyte depletion (hypokalemia, hypochloremia, hyponatremia) and dehydration resulting from excessive diuresis. If digitalis has also been administered, hypokalemia may accentuate cardiac arrhythmias.

Candesartan cannot be removed by hemodialysis. The degree to which hydrochlorothiazide is removed by hemodialysis has not been established.

Treatment

To obtain up-to-date information about the treatment of overdose, consult your Regional Poison Control Center. Telephone numbers of certified poison control centers are listed in the Physicians’ Desk Reference (PDR). In managing overdose, consider the possibilities of multiple-drug overdoses, drug-drug interactions, and altered pharmacokinetics in your patient.

DOSAGE AND ADMINISTRATION

The usual recommended starting dose of candesartan cilexetil is 16 mg once daily when it is used as monotherapy in patients who are not volume depleted. ATACAND can be administered once or twice daily with total daily doses ranging from 8 mg to 32 mg. Patients requiring further reduction in blood pressure should be titrated to 32 mg. Doses larger than 32 mg do not appear to have a greater blood pressure lowering effect.

Hydrochlorothiazide is effective in doses of 12.5 to 50 mg once daily.

Use in Renal Impairment: Dosing recommendations for ATACAND HCT in patients with creatinine clearance < 30 mg/min cannot be provided (see SPECIAL POPULATIONS, Renal Insufficiency).

Use in moderate to severe Hepatic Impairment: ATACAND HCT is not recommended for initiation because the appropriate starting dose, 8 mg, cannot be given (see SPECIAL POPULATIONS, Hepatic Insufficiency).

Replacement Therapy: The combination may be substituted for the titrated components.

Dose Titration by Clinical Effect: A patient whose blood pressure is not controlled on 25 mg of hydrochlorothiazide once daily can expect an incremental effect from ATACAND HCT 16-12.5 mg. A patient whose blood pressure is controlled on 25 mg of hydrochlorothiazide but is experiencing decreases in serum potassium can expect the same or incremental blood pressure effects from ATACAND HCT 16-12.5 mg and serum potassium may improve.

A patient whose blood pressure is not controlled on 32 mg of ATACAND can expect incremental blood pressure effects from ATACAND HCT 32-12.5 mg and then 32-25 mg. The maximal antihypertensive effect of any dose of ATACAND HCT can be expected within 4 weeks of initiating that dose.

ATACAND HCT may be administered with other antihypertensive agents.

ATACAND HCT may be administered with or without food.

HOW SUPPLIED

ATACAND HCT 16-12.5 mg Tablets are peach, oval, biconvex, non-film-coated tablets, scored on both sides and coded with ACS on one side. They are supplied in bottles of 90 tablets (NDC 62559-650-90).

ATACAND HCT 32-12.5 mg Tablets are yellow, oval, biconvex, non-film-coated tablets, scored on both sides and coded with ACJ on one side. They are supplied in bottles of 90 tablets (NDC 62559-651-90).

ATACAND HCT 32-25 mg Tablets are pink, oval, biconvex, non-film-coated tablets, scored on both sides and coded with ACD on one side. They are supplied in bottles of 90 tablets (NDC 62559-652-90).

Storage:

Store at 20° to 25°C (68° to 77°F); excursions permitted at 15° to 30°C (59° to 86°F) [see USP Controlled Room Temperature]. Keep container tightly closed.

Manufactured under the license from Takeda Pharmaceutical Company, Ltd.

Manufactured by:
AstraZeneca AB, SE-151 85
Södertälje, Sweden

Distributed by:
ANI Pharmaceuticals, Inc.
Baudette, MN 56623

ATACAND HCT is a registered trademark of the AstraZeneca group of companies and is licensed to ANI Pharmaceuticals.

10114 Rev 07/25

PRINCIPAL DISPLAY PANEL – 16 mg/12.5 mg

NDC 62559-650-90
ATACAND HCT® (candesartan cilexetil-hydrochlorothiazide) Tablets
16 mg/12.5 mg
Rx only
90 Tablets

PRINCIPAL DISPLAY PANEL – 32 mg/12.5 mg

NDC 62559-651-90
ATACAND HCT® (candesartan cilexetil-hydrochlorothiazide) Tablets
32 mg/12.5 mg
Rx only
90 Tablets

PRINCIPAL DISPLAY PANEL – 32 mg/25 mg

NDC 62559-652-90
ATACAND HCT® (candesartan cilexetil-hydrochlorothiazide) Tablets
32 mg/25 mg
Rx only
90 Tablets